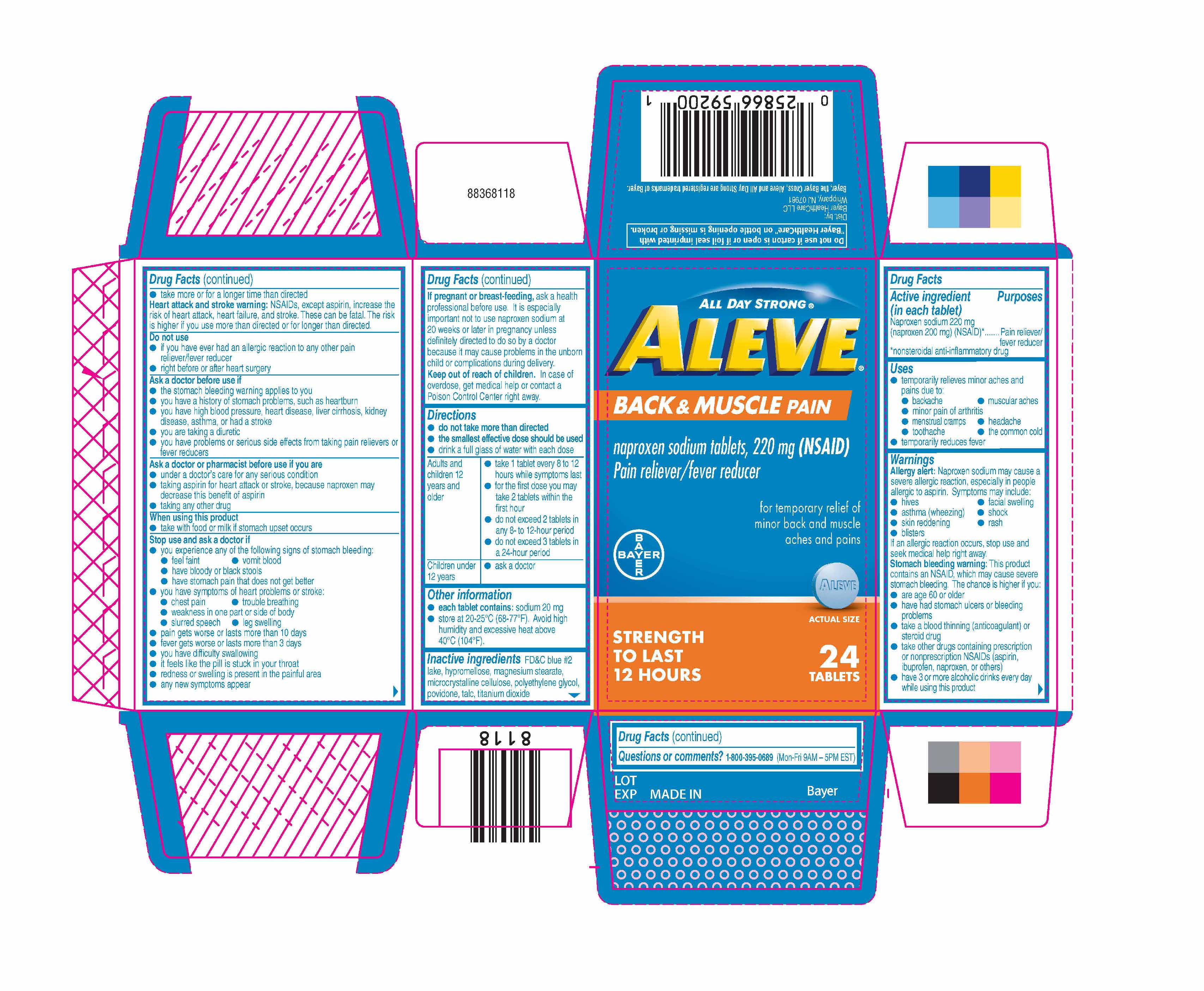 DRUG LABEL: Aleve Back and Muscle Pain
NDC: 0280-6092 | Form: TABLET
Manufacturer: Bayer HealthCare LLC.
Category: otc | Type: HUMAN OTC DRUG LABEL
Date: 20251204

ACTIVE INGREDIENTS: NAPROXEN SODIUM 220 mg/1 1
INACTIVE INGREDIENTS: MAGNESIUM STEARATE; TALC; TITANIUM DIOXIDE; POVIDONE; FD&C BLUE NO. 2; HYPROMELLOSES; MICROCRYSTALLINE CELLULOSE; POLYETHYLENE GLYCOL, UNSPECIFIED

Aleve Back & Muscle Pain UI 1600169

Drug Facts

Active ingredient (in each tablet)

Naproxen sodium 220 mg (naproxen 200 mg)

(NSAID)*

*nonsteroidal anti-inflammatory drug

Purposes

Pain reliever/fever reducer

Uses

- temporarily relieves minor aches and pains due to:
  - backache
  - muscular aches
  - minor pain of arthritis
  - menstrual cramps
  - headache
  - toothache
  - the common cold
- temporarily reduces fever

Directions

- do not take more than directed
- the smallest effective dose should be used
- drink a full glass of water with each dose

Adults and children 12 years and older | - take 1 tablets every 8 to 12 hours while symptoms last - for the first dose you may take 2 tablets within the first hour - do not exceed 2 tablets in any 8-to 12-hour period - do not exceed 3 tablets in a 24-hour period
Children under 12 years | - ask a doctor

Other information

- each tablet contains: sodium 20 mg
- store at 20-25ºC (68-77ºF). Avoid high humidity and excessive heat above 40°C (104°F).

INACTIVE INGREDIENT

Inactive ingredients FD&C blue #2 lake, hypromellose, magnesium stearate, microcrystalline cellulose, polyethylene glycol, povidone, talc, titanium dioxide

Questions or comments? 1-800-395-0689 (Mon – Fri 9AM – 5PM EST)

Dist. by :

Bayer Healthcare LLC

Whippany, NJ 07981

KEEP OUT OF REACH OF CHILDREN

In case of overdose, get medical help or contact a Poison Control Center right away.

Package label display

All Day Strong®

Aleve®

Back & Muscle Pain

naproxen sodium tablets, 220 mg (NSAID)

Pain reliever/fever reducer

Bayer

For temporary relief of minor back and muschle aches and pains

ACTUAL SIZE

Strength to Last 12 Hours 24Tablets